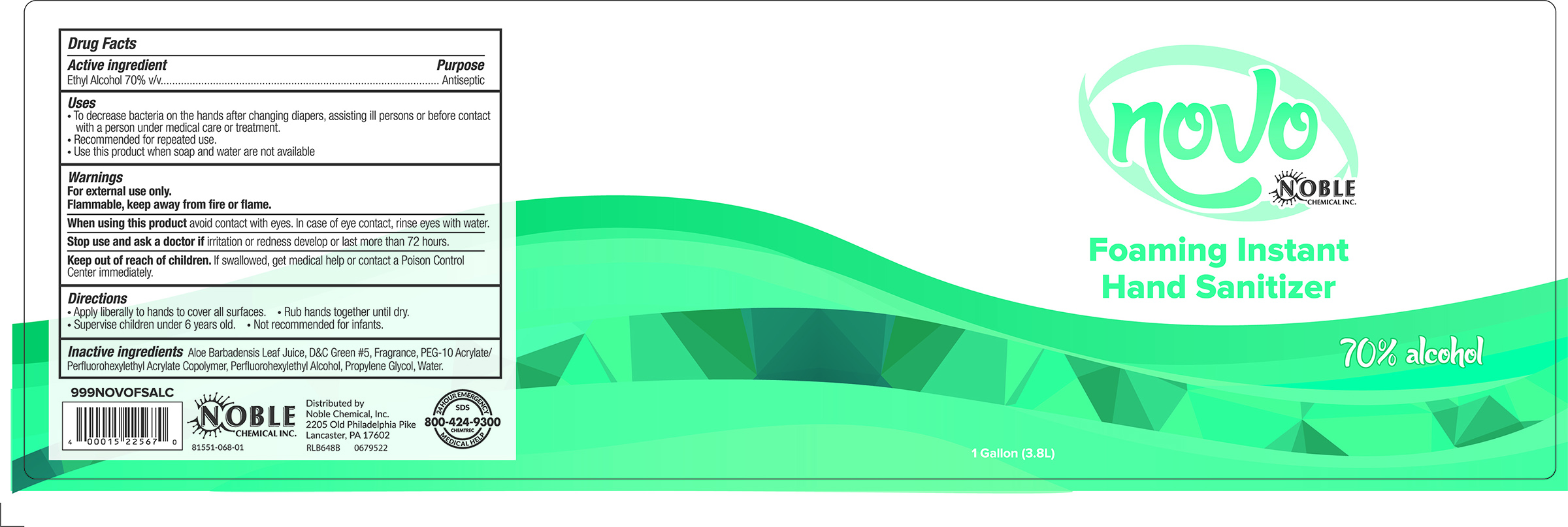 DRUG LABEL: Novo Foaming Instant Hand Sanitizer
NDC: 81551-802 | Form: LIQUID
Manufacturer: Noble Chemical Inc.
Category: otc | Type: HUMAN OTC DRUG LABEL
Date: 20251008

ACTIVE INGREDIENTS: ALCOHOL 0.7 mL/1 mL
INACTIVE INGREDIENTS: DIMETHICONE PEG-8 LAURATE 0.0113 mL/1 mL; WATER 0.27 mL/1 mL; EDETOL 0.0035 mL/1 mL; FRAGRANCE LEMON ORC2001060 0.0003 mL/1 mL; GLYCERIN 0.00113 mL/1 mL; CARBOMER INTERPOLYMER TYPE A (ALLYL SUCROSE CROSSLINKED) 0.0035 mL/1 mL; ALOE VERA LEAF 0.00001 mL/1 mL

Novo Foaming Instant Hand Sanitizer

active ingredient

Ethyl Alcohol 70% V/V

Inactive ingredient

Aloe Barbadensis leaf Juice, D&C Green #5, Fragrance, PEG-10 acrylate/perfluorohextl acrylate copolymer, Perfluorohexylethyl alcohol, Propylene Glycol, Water

dosage

Apply liberally to hands to cover all surfaces

Rub hands together until dry

Supervise children under 6 years old

Not recommended for infants

Indications

To decrease bacteria on hands when changing diapers,assiting ill persons or before contact with a person under medical care or treatment

Recommended for repeated use

Use this product when soap and water are not available

puepose

Antiseptic

Keep out of reach of children. If swallowed get medical help or contact poison control center immediately.

warnings

For external use only

Flammable, keep away from fire or flame

When using product avoid contact with eyes. In case of eye contact, rinse eyes with water

Stop use and ask doctor if irritation or redness develop or last more than 72 hours